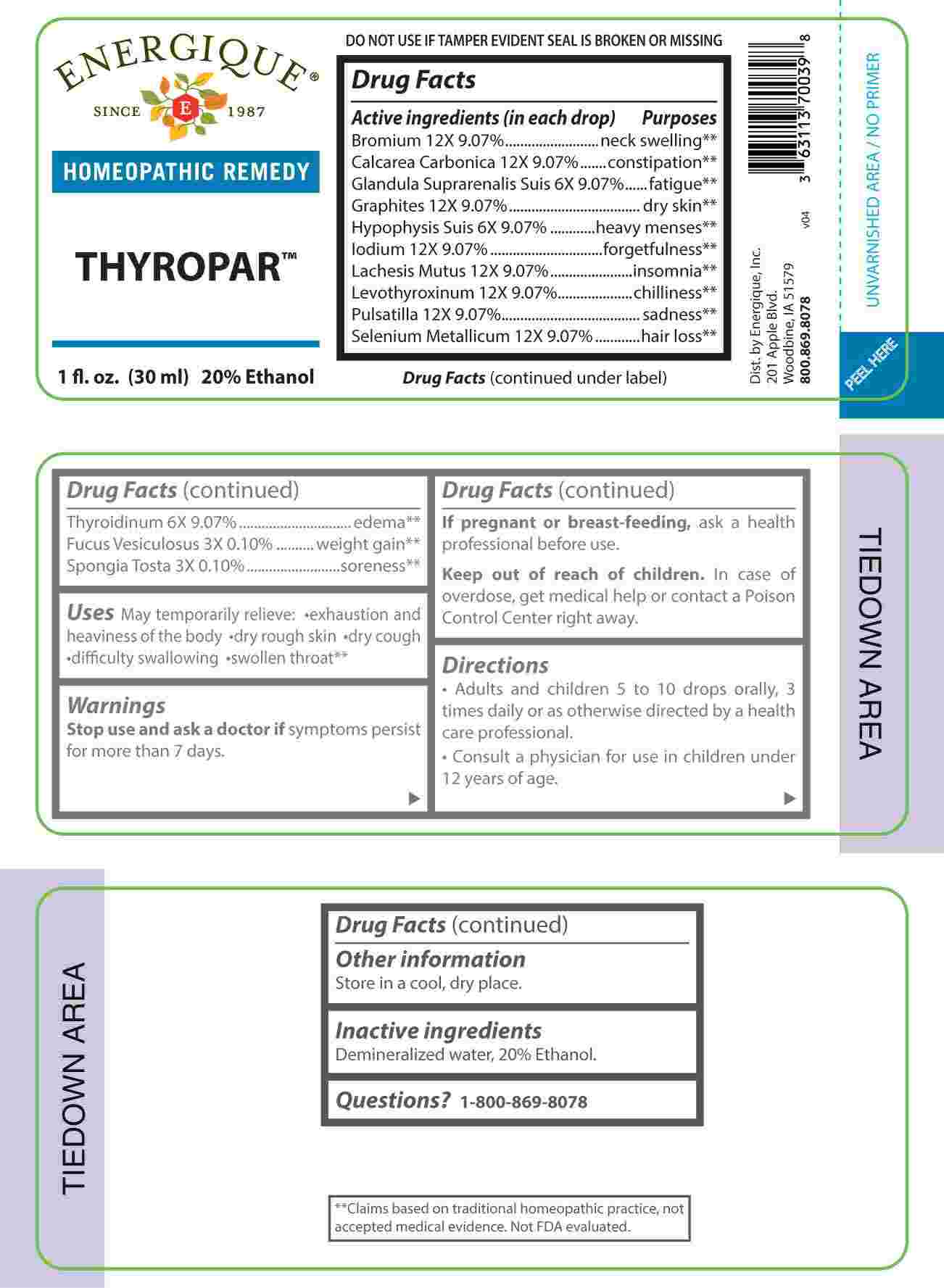 DRUG LABEL: Thyropar
NDC: 44911-0683 | Form: LIQUID
Manufacturer: Energique, Inc.
Category: homeopathic | Type: HUMAN OTC DRUG LABEL
Date: 20231026

ACTIVE INGREDIENTS: FUCUS VESICULOSUS 3 [hp_X]/1 mL; SPONGIA OFFICINALIS SKELETON, ROASTED 3 [hp_X]/1 mL; SUS SCROFA ADRENAL GLAND 6 [hp_X]/1 mL; SUS SCROFA PITUITARY GLAND 6 [hp_X]/1 mL; THYROID 6 [hp_X]/1 mL; BROMINE 12 [hp_X]/1 mL; OYSTER SHELL CALCIUM CARBONATE, CRUDE 12 [hp_X]/1 mL; GRAPHITE 12 [hp_X]/1 mL; IODINE 12 [hp_X]/1 mL; LACHESIS MUTA VENOM 12 [hp_X]/1 mL; LEVOTHYROXINE 12 [hp_X]/1 mL; PULSATILLA PRATENSIS WHOLE 12 [hp_X]/1 mL; SELENIUM 12 [hp_X]/1 mL
INACTIVE INGREDIENTS: WATER; ALCOHOL

DRUG FACTS:

ACTIVE INGREDIENTS:

(in each drop) Bromium 12X 9.07%, Calcarea Carbonica 12X 9.07%, Glandula Suprarenalis Suis 6X 9.07%, Graphites 12X 9.07%, Hypophysis Suis 6X 9.07%, Iodium 12X 9.07%, Lachesis Mutus 12X 9.07%, Levothyroxinum 12X 9.07%, Pulsatilla 12X 9.07%, Selenium Metallicum 12X 9.07%, Thyroidinum 6X 9.07%, Fucus Vesiculosus 3X 0.10%, Spongia Tosta 3X 0.10%.

PURPOSE:

Bromium – neck swelling,** Calcarea Carbonica 12X - constipation,** Glandula Suprarenalis Suis - fatigue,** Graphites – dry skin,** Hypophysis Suis – heavy menses,** Iodium - forgetfulness,** Lachesis Mutus - insomnia,** Levothyroxinum - chilliness,** Pulsatilla - sadness,** Selenium Metallicum – hair loss,** Thyroidinum - edema,** Fucus Vesiculosus – weight gain,** Spongia Tosta - soreness.**

**Claims based on traditional homeopathic practice, not accepted medical evidence. Not FDA evaluated.

USES:

May temporarily relieve: • exhaustion and heaviness of the body • dry rough skin • dry cough • difficulty swallowing • swollen throat.**

**Claims based on traditional homeopathic practice, not accepted medical evidence. Not FDA evaluated.

WARNINGS:

Stop use and ask a doctor if symptoms persist for more than 7 days.

If pregnant or breast-feeding, ask a health professional before use.

Keep out of reach of children. In case of overdose, get medical help or contact a Poison Control Center right away.

DO NOT USE IF TAMPER EVIDENT SEAL IS BROKEN OR MISSING

Store in a cool, dry place.

KEEP OUT OF REACH OF CHILDREN:

In case of overdose, get medical help or contact a Poison Control Center right away.

DIRECTIONS:

• Adults and children 5 to 10 drops orally, 3 times daily or as otherwise directed by a health care professional.

• Consult a physician for use in children under 12 years of age.

INACTIVE INGREDIENTS:

Demineralized water, 20% Ethanol.

QUESTIONS:

Dist. by Energique, Inc.

201 Apple Blvd.

Woodbine, IA 51579 800.869.8078

PACKAGE LABEL DISPLAY:

ENERGIQUE
SINCE 1987
HOMEOPATHIC REMEDY
THYROPAR
1 fl. oz. (30 ml)